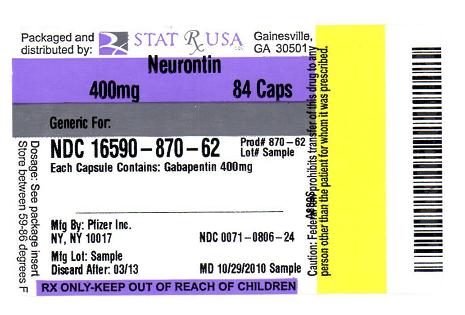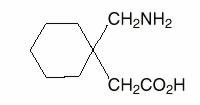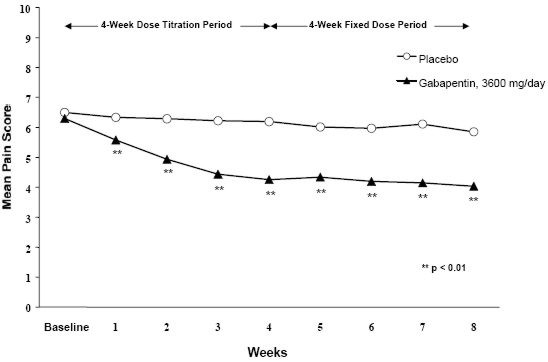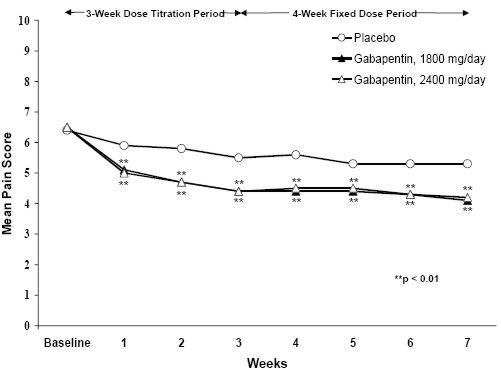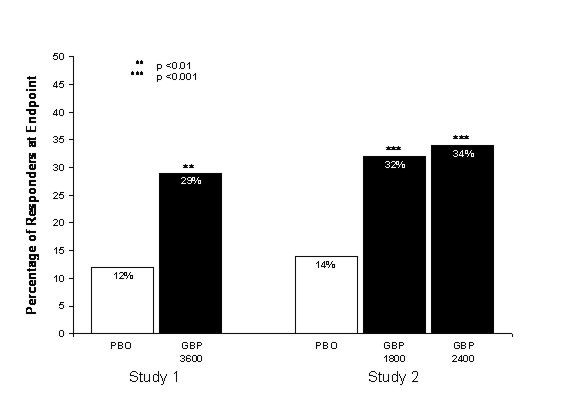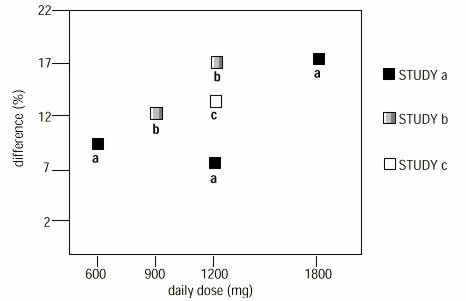 DRUG LABEL: Neurontin
NDC: 16590-870 | Form: CAPSULE
Manufacturer: STAT RX USA LLC
Category: prescription | Type: HUMAN PRESCRIPTION DRUG LABEL
Date: 20101105

ACTIVE INGREDIENTS: Gabapentin 400 mg/1 1
INACTIVE INGREDIENTS: lactose; starch, corn; talc; gelatin; ferric oxide red; titanium dioxide; ferric oxide yellow; FD&C BLUE NO. 2

Neurontin® (gabapentin) Capsules
Neurontin® (gabapentin) Tablets
Neurontin®(gabapentin) Oral Solution

DESCRIPTION

Neurontin® (gabapentin) Capsules, Neurontin® (gabapentin) Tablets, and Neurontin® (gabapentin) Oral Solution are supplied as imprinted hard shell capsules containing 100 mg, 300 mg, and 400 mg of gabapentin, elliptical film-coated tablets containing 600 mg and 800 mg of gabapentin or an oral solution containing 250 mg/5 mL of gabapentin.

The inactive ingredients for the capsules are lactose, cornstarch, and talc. The 100 mg capsule shell contains gelatin and titanium dioxide. The 300 mg capsule shell contains gelatin, titanium dioxide, and yellow iron oxide. The 400 mg capsule shell contains gelatin, red iron oxide, titanium dioxide, and yellow iron oxide. The imprinting ink contains FD&C Blue No. 2 and titanium dioxide.

The inactive ingredients for the tablets are poloxamer 407, copolyvidonum, cornstarch, magnesium stearate, hydroxypropyl cellulose, talc, candelilla wax and purified water.

The inactive ingredients for the oral solution are glycerin, xylitol, purified water and artificial cool strawberry anise flavor.

Gabapentin is described as 1-(aminomethyl)cyclohexaneacetic acid with a molecular formula of C9H17NO2 and a molecular weight of 171.24. The structural formula of gabapentin is:

Gabapentin is a white to off-white crystalline solid with a pKa1 of 3.7 and a pKa2 of 10.7. It is freely soluble in water and both basic and acidic aqueous solutions. The log of the partition coefficient (n-octanol/0.05M phosphate buffer) at pH 7.4 is –1.25.

CLINICAL PHARMACOLOGY

Mechanism of Action

The mechanism by which gabapentin exerts its analgesic action is unknown, but in animal models of analgesia, gabapentin prevents allodynia (pain-related behavior in response to a normally innocuous stimulus) and hyperalgesia (exaggerated response to painful stimuli). In particular, gabapentin prevents pain-related responses in several models of neuropathic pain in rats or mice (e.g. spinal nerve ligation models, streptozocin-induced diabetes model, spinal cord injury model, acute herpes zoster infection model). Gabapentin also decreases pain-related responses after peripheral inflammation (carrageenan footpad test, late phase of formalin test). Gabapentin did not alter immediate pain-related behaviors (rat tail flick test, formalin footpad acute phase, acetic acid abdominal constriction test, footpad heat irradiation test). The relevance of these models to human pain is not known.

The mechanism by which gabapentin exerts its anticonvulsant action is unknown, but in animal test systems designed to detect anticonvulsant activity, gabapentin prevents seizures as do other marketed anticonvulsants. Gabapentin exhibits antiseizure activity in mice and rats in both the maximal electroshock and pentylenetetrazole seizure models and other preclinical models (e.g., strains with genetic epilepsy, etc.). The relevance of these models to human epilepsy is not known.

Gabapentin is structurally related to the neurotransmitter GABA (gamma-aminobutyric acid) but it does not modify GABAA or GABAB radioligand binding, it is not converted metabolically into GABA or a GABA agonist, and it is not an inhibitor of GABA uptake or degradation. Gabapentin was tested in radioligand binding assays at concentrations up to 100 µM and did not exhibit affinity for a number of other common receptor sites, including benzodiazepine, glutamate, N-methyl-D-aspartate (NMDA), quisqualate, kainate, strychnine-insensitive or strychnine-sensitive glycine, alpha 1, alpha 2, or beta adrenergic, adenosine A1 or A2, cholinergic muscarinic or nicotinic, dopamine D1 or D2, histamine H1, serotonin S1 or S2, opiate mu, delta or kappa, cannabinoid 1, voltage-sensitive calcium channel sites labeled with nitrendipine or diltiazem, or at voltage-sensitive sodium channel sites labeled with batrachotoxinin A 20-alpha-benzoate. Furthermore, gabapentin did not alter the cellular uptake of dopamine, noradrenaline, or serotonin.

In vitro studies with radiolabeled gabapentin have revealed a gabapentin binding site in areas of rat brain including neocortex and hippocampus. A high-affinity binding protein in animal brain tissue has been identified as an auxiliary subunit of voltage-activated calcium channels. However, functional correlates of gabapentin binding, if any, remain to be elucidated.

Pharmacokinetics and Drug Metabolism

All pharmacological actions following gabapentin administration are due to the activity of the parent compound; gabapentin is not appreciably metabolized in humans.

Oral Bioavailability

Gabapentin bioavailability is not dose proportional; i.e., as dose is increased, bioavailability decreases. Bioavailability of gabapentin is approximately 60%, 47%, 34%, 33%, and 27% following 900, 1200, 2400, 3600, and 4800 mg/day given in 3 divided doses, respectively. Food has only a slight effect on the rate and extent of absorption of gabapentin (14% increase in AUC and Cmax).

Distribution

Less than 3% of gabapentin circulates bound to plasma protein. The apparent volume of distribution of gabapentin after 150 mg intravenous administration is 58±6 L (Mean ±SD). In patients with epilepsy, steady-state predose (Cmin) concentrations of gabapentin in cerebrospinal fluid were approximately 20% of the corresponding plasma concentrations.

Elimination

Gabapentin is eliminated from the systemic circulation by renal excretion as unchanged drug. Gabapentin is not appreciably metabolized in humans.

Gabapentin elimination half-life is 5 to 7 hours and is unaltered by dose or following multiple dosing. Gabapentin elimination rate constant, plasma clearance, and renal clearance are directly proportional to creatinine clearance (see Special Populations: Patients With Renal Insufficiency, below). In elderly patients, and in patients with impaired renal function, gabapentin plasma clearance is reduced. Gabapentin can be removed from plasma by hemodialysis.

Dosage adjustment in patients with compromised renal function or undergoing hemodialysis is recommended (see DOSAGE AND ADMINISTRATION, Table 6).

Special Populations

Adult Patients With Renal Insufficiency

Subjects (N=60) with renal insufficiency (mean creatinine clearance ranging from 13–114 mL/min) were administered single 400 mg oral doses of gabapentin. The mean gabapentin half-life ranged from about 6.5 hours (patients with creatinine clearance >60 mL/min) to 52 hours (creatinine clearance <30 mL/min) and gabapentin renal clearance from about 90 mL/min (>60 mL/min group) to about 10 mL/min (<30 mL/min). Mean plasma clearance (CL/F) decreased from approximately 190 mL/min to 20 mL/min.

Dosage adjustment in adult patients with compromised renal function is necessary (see DOSAGE AND ADMINISTRATION). Pediatric patients with renal insufficiency have not been studied.

Hemodialysis

In a study in anuric adult subjects (N=11), the apparent elimination half-life of gabapentin on nondialysis days was about 132 hours; during dialysis the apparent half-life of gabapentin was reduced to 3.8 hours. Hemodialysis thus has a significant effect on gabapentin elimination in anuric subjects.

Dosage adjustment in patients undergoing hemodialysis is necessary (see DOSAGE AND ADMINISTRATION).

Hepatic Disease

Because gabapentin is not metabolized, no study was performed in patients with hepatic impairment.

Age

The effect of age was studied in subjects 20–80 years of age. Apparent oral clearance (CL/F) of gabapentin decreased as age increased, from about 225 mL/min in those under 30 years of age to about 125 mL/min in those over 70 years of age. Renal clearance (CLr) and CLr adjusted for body surface area also declined with age; however, the decline in the renal clearance of gabapentin with age can largely be explained by the decline in renal function. Reduction of gabapentin dose may be required in patients who have age related compromised renal function. (See PRECAUTIONS, Geriatric Use, and DOSAGE AND ADMINISTRATION.)

Pediatric

Gabapentin pharmacokinetics were determined in 48 pediatric subjects between the ages of 1 month and 12 years following a dose of approximately 10 mg/kg. Peak plasma concentrations were similar across the entire age group and occurred 2 to 3 hours postdose. In general, pediatric subjects between 1 month and <5 years of age achieved approximately 30% lower exposure (AUC) than that observed in those 5 years of age and older. Accordingly, oral clearance normalized per body weight was higher in the younger children. Apparent oral clearance of gabapentin was directly proportional to creatinine clearance. Gabapentin elimination half-life averaged 4.7 hours and was similar across the age groups studied.

A population pharmacokinetic analysis was performed in 253 pediatric subjects between 1 month and 13 years of age. Patients received 10 to 65 mg/kg/day given TID. Apparent oral clearance (CL/F) was directly proportional to creatinine clearance and this relationship was similar following a single dose and at steady state. Higher oral clearance values were observed in children <5 years of age compared to those observed in children 5 years of age and older, when normalized per body weight. The clearance was highly variable in infants <1 year of age. The normalized CL/F values observed in pediatric patients 5 years of age and older were consistent with values observed in adults after a single dose. The oral volume of distribution normalized per body weight was constant across the age range.

These pharmacokinetic data indicate that the effective daily dose in pediatric patients with epilepsy ages 3 and 4 years should be 40 mg/kg/day to achieve average plasma concentrations similar to those achieved in patients 5 years of age and older receiving gabapentin at 30 mg/kg/day (see DOSAGE AND ADMINISTRATION).

Gender

Although no formal study has been conducted to compare the pharmacokinetics of gabapentin in men and women, it appears that the pharmacokinetic parameters for males and females are similar and there are no significant gender differences.

Race

Pharmacokinetic differences due to race have not been studied. Because gabapentin is primarily renally excreted and there are no important racial differences in creatinine clearance, pharmacokinetic differences due to race are not expected.

Clinical Studies

Postherpetic Neuralgia

Neurontin was evaluated for the management of postherpetic neuralgia (PHN) in 2 randomized, double-blind, placebo-controlled, multicenter studies; N=563 patients in the intent-to-treat (ITT) population (Table 1). Patients were enrolled if they continued to have pain for more than 3 months after healing of the herpes zoster skin rash.

TABLE 1. Controlled PHN Studies: Duration, Dosages, and Number of Patients
Study | Study Duration | Gabapentin (mg/day) [Given in 3 divided doses (TID)] Target Dose | Patients Receiving Gabapentin | Patients Receiving Placebo
1 | 8 weeks | 3600 | 113 | 116
2 | 7 weeks | 1800, 2400 | 223 | 111
Total |  |  | 336 | 227

Each study included a 1-week baseline during which patients were screened for eligibility and a 7- or 8-week double-blind phase (3 or 4 weeks of titration and 4 weeks of fixed dose). Patients initiated treatment with titration to a maximum of 900 mg/day gabapentin over 3 days. Dosages were then to be titrated in 600 to 1200 mg/day increments at 3- to 7-day intervals to target dose over 3 to 4 weeks. In Study 1, patients were continued on lower doses if not able to achieve the target dose. During baseline and treatment, patients recorded their pain in a daily diary using an 11-point numeric pain rating scale ranging from 0 (no pain) to 10 (worst possible pain). A mean pain score during baseline of at least 4 was required for randomization (baseline mean pain score for Studies 1 and 2 combined was 6.4). Analyses were conducted using the ITT population (all randomized patients who received at least one dose of study medication).

Both studies showed significant differences from placebo at all doses tested.

A significant reduction in weekly mean pain scores was seen by Week 1 in both studies, and significant differences were maintained to the end of treatment. Comparable treatment effects were observed in all active treatment arms. Pharmacokinetic/pharmacodynamic modeling provided confirmatory evidence of efficacy across all doses. Figures 1 and 2 show these changes for Studies 1 and 2.

Figure 1. Weekly Mean Pain Scores (Observed Cases in ITT Population): Study 1

Figure 2. Weekly Mean Pain Scores (Observed Cases in ITT Population): Study 2

The proportion of responders (those patients reporting at least 50% improvement in endpoint pain score compared with baseline) was calculated for each study (Figure 3).

Figure 3. Proportion of Responders (patients with ≥50% reduction in pain score) at Endpoint: Controlled PHN Studies

Epilepsy

The effectiveness of Neurontin as adjunctive therapy (added to other antiepileptic drugs) was established in multicenter placebo-controlled, double-blind, parallel-group clinical trials in adult and pediatric patients (3 years and older) with refractory partial seizures.

Evidence of effectiveness was obtained in three trials conducted in 705 patients (age 12 years and above) and one trial conducted in 247 pediatric patients (3 to 12 years of age). The patients enrolled had a history of at least 4 partial seizures per month in spite of receiving one or more antiepileptic drugs at therapeutic levels and were observed on their established antiepileptic drug regimen during a 12-week baseline period (6 weeks in the study of pediatric patients). In patients continuing to have at least 2 (or 4 in some studies) seizures per month, Neurontin or placebo was then added on to the existing therapy during a 12-week treatment period. Effectiveness was assessed primarily on the basis of the percent of patients with a 50% or greater reduction in seizure frequency from baseline to treatment (the "responder rate") and a derived measure called response ratio, a measure of change defined as (T – B)/(T + B), where B is the patient''s baseline seizure frequency and T is the patient's seizure frequency during treatment. Response ratio is distributed within the range –1 to +1. A zero value indicates no change while complete elimination of seizures would give a value of –1; increased seizure rates would give positive values. A response ratio of –0.33 corresponds to a 50% reduction in seizure frequency. The results given below are for all partial seizures in the intent-to-treat (all patients who received any doses of treatment) population in each study, unless otherwise indicated.

One study compared Neurontin 1200 mg/day divided TID with placebo. Responder rate was 23% (14/61) in the Neurontin group and 9% (6/66) in the placebo group; the difference between groups was statistically significant. Response ratio was also better in the Neurontin group (–0.199) than in the placebo group (–0.044), a difference that also achieved statistical significance.

A second study compared primarily 1200 mg/day divided TID Neurontin (N=101) with placebo (N=98). Additional smaller Neurontin dosage groups (600 mg/day, N=53; 1800 mg/day, N=54) were also studied for information regarding dose response. Responder rate was higher in the Neurontin 1200 mg/day group (16%) than in the placebo group (8%), but the difference was not statistically significant. The responder rate at 600 mg (17%) was also not significantly higher than in the placebo, but the responder rate in the 1800 mg group (26%) was statistically significantly superior to the placebo rate. Response ratio was better in the Neurontin 1200 mg/day group (–0.103) than in the placebo group (–0.022); but this difference was also not statistically significant (p = 0.224). A better response was seen in the Neurontin 600 mg/day group (–0.105) and 1800 mg/day group (–0.222) than in the 1200 mg/day group, with the 1800 mg/day group achieving statistical significance compared to the placebo group.

A third study compared Neurontin 900 mg/day divided TID (N=111) and placebo (N=109). An additional Neurontin 1200 mg/day dosage group (N=52) provided dose-response data. A statistically significant difference in responder rate was seen in the Neurontin 900 mg/day group (22%) compared to that in the placebo group (10%). Response ratio was also statistically significantly superior in the Neurontin 900 mg/day group (–0.119) compared to that in the placebo group (–0.027), as was response ratio in 1200 mg/day Neurontin (–0.184) compared to placebo.

Analyses were also performed in each study to examine the effect of Neurontin on preventing secondarily generalized tonic-clonic seizures. Patients who experienced a secondarily generalized tonic-clonic seizure in either the baseline or in the treatment period in all three placebo-controlled studies were included in these analyses. There were several response ratio comparisons that showed a statistically significant advantage for Neurontin compared to placebo and favorable trends for almost all comparisons.

Analysis of responder rate using combined data from all three studies and all doses (N=162, Neurontin; N=89, placebo) also showed a significant advantage for Neurontin over placebo in reducing the frequency of secondarily generalized tonic-clonic seizures.

In two of the three controlled studies, more than one dose of Neurontin was used. Within each study the results did not show a consistently increased response to dose. However, looking across studies, a trend toward increasing efficacy with increasing dose is evident (see Figure 4).

Figure 4. Responder Rate in Patients Receiving Neurontin Expressed as a Difference from Placebo by Dose and Study: Adjunctive Therapy Studies in Patients ≥12 Years of Age with Partial Seizures

In the figure, treatment effect magnitude, measured on the Y axis in terms of the difference in the proportion of gabapentin and placebo assigned patients attaining a 50% or greater reduction in seizure frequency from baseline, is plotted against the daily dose of gabapentin administered (X axis).

Although no formal analysis by gender has been performed, estimates of response (Response Ratio) derived from clinical trials (398 men, 307 women) indicate no important gender differences exist. There was no consistent pattern indicating that age had any effect on the response to Neurontin. There were insufficient numbers of patients of races other than Caucasian to permit a comparison of efficacy among racial groups.

A fourth study in pediatric patients age 3 to 12 years compared 25 – 35 mg/kg/day Neurontin (N=118) with placebo (N=127). For all partial seizures in the intent-to-treat population, the response ratio was statistically significantly better for the Neurontin group (–0.146) than for the placebo group (–0.079). For the same population, the responder rate for Neurontin (21%) was not significantly different from placebo (18%).

A study in pediatric patients age 1 month to 3 years compared 40 mg/kg/day Neurontin (N=38) with placebo (N=38) in patients who were receiving at least one marketed antiepileptic drug and had at least one partial seizure during the screening period (within 2 weeks prior to baseline). Patients had up to 48 hours of baseline and up to 72 hours of double-blind video EEG monitoring to record and count the occurrence of seizures. There were no statistically significant differences between treatments in either the response ratio or responder rate.

INDICATIONS AND USAGE

Postherpetic Neuralgia

Neurontin (gabapentin) is indicated for the management of postherpetic neuralgia in adults.

Epilepsy

Neurontin (gabapentin) is indicated as adjunctive therapy in the treatment of partial seizures with and without secondary generalization in patients over 12 years of age with epilepsy. Neurontin is also indicated as adjunctive therapy in the treatment of partial seizures in pediatric patients age 3 – 12 years.

CONTRAINDICATIONS

Neurontin is contraindicated in patients who have demonstrated hypersensitivity to the drug or its ingredients.

WARNINGS

Suicidal Behavior and Ideation

Antiepileptic drugs (AEDs), including Neurontin, increase the risk of suicidal thoughts or behavior in patients taking these drugs for any indication. Patients treated with any AED for any indication should be monitored for the emergence or worsening of depression, suicidal thoughts or behavior, and/or any unusual changes in mood or behavior.

Pooled analyses of 199 placebo-controlled clinical trials (mono- and adjunctive therapy) of 11 different AEDs showed that patients randomized to one of the AEDs had approximately twice the risk (adjusted Relative Risk 1.8, 95% CI:1.2, 2.7) of suicidal thinking or behavior compared to patients randomized to placebo. In these trials, which had a median treatment duration of 12 weeks, the estimated incidence rate of suicidal behavior or ideation among 27,863 AED-treated patients was 0.43%, compared to 0.24% among 16,029 placebo-treated patients, representing an increase of approximately one case of suicidal thinking or behavior for every 530 patients treated. There were four suicides in drug-treated patients in the trials and none in placebo-treated patients, but the number is too small to allow any conclusion about drug effect on suicide.

The increased risk of suicidal thoughts or behavior with AEDs was observed as early as one week after starting drug treatment with AEDs and persisted for the duration of treatment assessed. Because most trials included in the analysis did not extend beyond 24 weeks, the risk of suicidal thoughts or behavior beyond 24 weeks could not be assessed.

The risk of suicidal thoughts or behavior was generally consistent among drugs in the data analyzed. The finding of increased risk with AEDs of varying mechanisms of action and across a range of indications suggests that the risk applies to all AEDs used for any indication. The risk did not vary substantially by age (5-100 years) in the clinical trials analyzed.

Table 2 shows absolute and relative risk by indication for all evaluated AEDs.

Table 2 Risk by indication for antiepileptic drugs in the pooled analysis
Indication | Placebo Patients with Events Per 1000 Patients | Drug Patients with Events Per 1000 Patients | Relative Risk: Incidence of Events in Drug Patients/Incidence in Placebo Patients | Risk Difference: Additional Drug Patients with Events Per 1000 Patients
Epilepsy | 1.0 | 3.4 | 3.5 | 2.4
Psychiatric | 5.7 | 8.5 | 1.5 | 2.9
Other | 1.0 | 1.8 | 1.9 | 0.9
Total | 2.4 | 4.3 | 1.8 | 1.9

The relative risk for suicidal thoughts or behavior was higher in clinical trials for epilepsy than in clinical trials for psychiatric or other conditions, but the absolute risk differences were similar for the epilepsy and psychiatric indications.

Anyone considering prescribing Neurontin or any other AED must balance the risk of suicidal thoughts or behavior with the risk of untreated illness. Epilepsy and many other illnesses for which AEDs are prescribed are themselves associated with morbidity and mortality and an increased risk of suicidal thoughts and behavior. Should suicidal thoughts and behavior emerge during treatment, the prescriber needs to consider whether the emergence of these symptoms in any given patient may be related to the illness being treated.

Patients, their caregivers, and families should be informed that AEDs increase the risk of suicidal thoughts and behavior and should be advised of the need to be alert for the emergence or worsening of the signs and symptoms of depression, any unusual changes in mood or behavior, or the emergence of suicidal thoughts, behavior, or thoughts about self-harm. Behaviors of concern should be reported immediately to healthcare providers.

Neuropsychiatric Adverse Events—Pediatric Patients 3–12 years of age

Gabapentin use in pediatric patients with epilepsy 3–12 years of age is associated with the occurrence of central nervous system related adverse events. The most significant of these can be classified into the following categories: 1) emotional lability (primarily behavioral problems), 2) hostility, including aggressive behaviors, 3) thought disorder, including concentration problems and change in school performance, and 4) hyperkinesia (primarily restlessness and hyperactivity). Among the gabapentin-treated patients, most of the events were mild to moderate in intensity.

In controlled trials in pediatric patients 3–12 years of age the incidence of these adverse events was: emotional lability 6% (gabapentin-treated patients) vs 1.3% (placebo-treated patients); hostility 5.2% vs 1.3%; hyperkinesia 4.7% vs 2.9%; and thought disorder 1.7% vs 0%. One of these events, a report of hostility, was considered serious. Discontinuation of gabapentin treatment occurred in 1.3% of patients reporting emotional lability and hyperkinesia and 0.9% of gabapentin-treated patients reporting hostility and thought disorder. One placebo-treated patient (0.4%) withdrew due to emotional lability.

Withdrawal Precipitated Seizure, Status Epilepticus

Antiepileptic drugs should not be abruptly discontinued because of the possibility of increasing seizure frequency.

In the placebo-controlled studies in patients >12 years of age, the incidence of status epilepticus in patients receiving Neurontin was 0.6% (3 of 543) versus 0.5% in patients receiving placebo (2 of 378). Among the 2074 patients >12 years of age treated with Neurontin across all studies (controlled and uncontrolled) 31 (1.5%) had status epilepticus. Of these, 14 patients had no prior history of status epilepticus either before treatment or while on other medications. Because adequate historical data are not available, it is impossible to say whether or not treatment with Neurontin is associated with a higher or lower rate of status epilepticus than would be expected to occur in a similar population not treated with Neurontin.

Tumorigenic Potential

In standard preclinical in vivo lifetime carcinogenicity studies, an unexpectedly high incidence of pancreatic acinar adenocarcinomas was identified in male, but not female, rats. (See PRECAUTIONS: Carcinogenesis, Mutagenesis, Impairment of Fertility.) The clinical significance of this finding is unknown. Clinical experience during gabapentin's premarketing development provides no direct means to assess its potential for inducing tumors in humans.

In clinical studies in adjunctive therapy in epilepsy comprising 2085 patient-years of exposure in patients >12 years of age, new tumors were reported in 10 patients (2 breast, 3 brain, 2 lung, 1 adrenal, 1 non-Hodgkin's lymphoma, 1 endometrial carcinoma in situ), and preexisting tumors worsened in 11 patients (9 brain, 1 breast, 1 prostate) during or up to 2 years following discontinuation of Neurontin. Without knowledge of the background incidence and recurrence in a similar population not treated with Neurontin, it is impossible to know whether the incidence seen in this cohort is or is not affected by treatment.

Sudden and Unexplained Death in Patients With Epilepsy

During the course of premarketing development of Neurontin 8 sudden and unexplained deaths were recorded among a cohort of 2203 patients treated (2103 patient-years of exposure).

Some of these could represent seizure-related deaths in which the seizure was not observed, e.g., at night. This represents an incidence of 0.0038 deaths per patient-year. Although this rate exceeds that expected in a healthy population matched for age and sex, it is within the range of estimates for the incidence of sudden unexplained deaths in patients with epilepsy not receiving Neurontin (ranging from 0.0005 for the general population of epileptics to 0.003 for a clinical trial population similar to that in the Neurontin program, to 0.005 for patients with refractory epilepsy). Consequently, whether these figures are reassuring or raise further concern depends on comparability of the populations reported upon to the Neurontin cohort and the accuracy of the estimates provided.

PRECAUTIONS

Information for Patients

Patients should be instructed to take Neurontin only as prescribed.

Patients, their caregivers, and families should be counseled that AEDs, including Neurontin, may increase the risk of suicidal thoughts and behavior and should be advised of the need to be alert for the emergence or worsening of symptoms of depression, any unusual changes in mood or behavior, or the emergence of suicidal thoughts, behavior, or thoughts about self-harm. Behaviors of concern should be reported immediately to healthcare providers.

Patients should be advised that Neurontin may cause dizziness, somnolence and other symptoms and signs of CNS depression. Accordingly, they should be advised neither to drive a car nor to operate other complex machinery until they have gained sufficient experience on Neurontin to gauge whether or not it affects their mental and/or motor performance adversely.

Patients who require concomitant treatment with morphine may experience increases in gabapentin concentrations. Patients should be carefully observed for signs of CNS depression, such as somnolence, and the dose of Neurontin or morphine should be reduced appropriately (see Drug Interactions).

Patients should be encouraged to enroll in the North American Antiepileptic Drug (NAAED) Pregnancy Registry if they become pregnant. This registry is collecting information about the safety of antiepileptic drugs during pregnancy. To enroll, patients can call the toll free number 1-888-233-2334 (see PRECAUTIONS, Pregnancy section).

Laboratory Tests

Clinical trials data do not indicate that routine monitoring of clinical laboratory parameters is necessary for the safe use of Neurontin. The value of monitoring gabapentin blood concentrations has not been established. Neurontin may be used in combination with other antiepileptic drugs without concern for alteration of the blood concentrations of gabapentin or of other antiepileptic drugs.

Drug Interactions

In vitro studies were conducted to investigate the potential of gabapentin to inhibit the major cytochrome P450 enzymes (CYP1A2, CYP2A6, CYP2C9, CYP2C19, CYP2D6, CYP2E1, and CYP3A4) that mediate drug and xenobiotic metabolism using isoform selective marker substrates and human liver microsomal preparations. Only at the highest concentration tested (171 µg/mL; 1 mM) was a slight degree of inhibition (14%–30%) of isoform CYP2A6 observed. No inhibition of any of the other isoforms tested was observed at gabapentin concentrations up to 171 µg/mL (approximately 15 times the Cmax at 3600 mg/day).

Gabapentin is not appreciably metabolized nor does it interfere with the metabolism of commonly coadministered antiepileptic drugs.

The drug interaction data described in this section were obtained from studies involving healthy adults and adult patients with epilepsy.

Phenytoin

In a single (400 mg) and multiple dose (400 mg TID) study of Neurontin in epileptic patients (N=8) maintained on phenytoin monotherapy for at least 2 months, gabapentin had no effect on the steady-state trough plasma concentrations of phenytoin and phenytoin had no effect on gabapentin pharmacokinetics.

Carbamazepine

Steady-state trough plasma carbamazepine and carbamazepine 10, 11 epoxide concentrations were not affected by concomitant gabapentin (400 mg TID; N=12) administration. Likewise, gabapentin pharmacokinetics were unaltered by carbamazepine administration.

Valproic Acid

The mean steady-state trough serum valproic acid concentrations prior to and during concomitant gabapentin administration (400 mg TID; N=17) were not different and neither were gabapentin pharmacokinetic parameters affected by valproic acid.

Phenobarbital

Estimates of steady-state pharmacokinetic parameters for phenobarbital or gabapentin (300 mg TID; N=12) are identical whether the drugs are administered alone or together.

Naproxen

Coadministration (N=18) of naproxen sodium capsules (250 mg) with Neurontin (125 mg) appears to increase the amount of gabapentin absorbed by 12% to 15%. Gabapentin had no effect on naproxen pharmacokinetic parameters. These doses are lower than the therapeutic doses for both drugs. The magnitude of interaction within the recommended dose ranges of either drug is not known.

Hydrocodone

Coadministration of Neurontin (125 to 500 mg; N=48) decreases hydrocodone (10 mg; N=50) Cmax and AUC values in a dose-dependent manner relative to administration of hydrocodone alone; Cmax and AUC values are 3% to 4% lower, respectively, after administration of 125 mg Neurontin and 21% to 22% lower, respectively, after administration of 500 mg Neurontin. The mechanism for this interaction is unknown. Hydrocodone increases gabapentin AUC values by 14%. The magnitude of interaction at other doses is not known.

Morphine

A literature article reported that when a 60-mg controlled-release morphine capsule was administered 2 hours prior to a 600-mg Neurontin capsule (N=12), mean gabapentin AUC increased by 44% compared to gabapentin administered without morphine (see PRECAUTIONS). Morphine pharmacokinetic parameter values were not affected by administration of Neurontin 2 hours after morphine. The magnitude of interaction at other doses is not known.

Cimetidine

In the presence of cimetidine at 300 mg QID (N=12) the mean apparent oral clearance of gabapentin fell by 14% and creatinine clearance fell by 10%. Thus cimetidine appeared to alter the renal excretion of both gabapentin and creatinine, an endogenous marker of renal function. This small decrease in excretion of gabapentin by cimetidine is not expected to be of clinical importance. The effect of gabapentin on cimetidine was not evaluated.

Oral Contraceptive

Based on AUC and half-life, multiple-dose pharmacokinetic profiles of norethindrone and ethinyl estradiol following administration of tablets containing 2.5 mg of norethindrone acetate and 50 mcg of ethinyl estradiol were similar with and without coadministration of gabapentin (400 mg TID; N=13). The Cmax of norethindrone was 13% higher when it was coadministered with gabapentin; this interaction is not expected to be of clinical importance.

Antacid (Maalox®)

Maalox reduced the bioavailability of gabapentin (N=16) by about 20%. This decrease in bioavailability was about 5% when gabapentin was administered 2 hours after Maalox. It is recommended that gabapentin be taken at least 2 hours following Maalox administration.

Effect of Probenecid

Probenecid is a blocker of renal tubular secretion. Gabapentin pharmacokinetic parameters without and with probenecid were comparable. This indicates that gabapentin does not undergo renal tubular secretion by the pathway that is blocked by probenecid.

Drug/Laboratory Tests Interactions

Because false positive readings were reported with the Ames N-Multistix SG® dipstick test for urinary protein when gabapentin was added to other antiepileptic drugs, the more specific sulfosalicylic acid precipitation procedure is recommended to determine the presence of urine protein.

Carcinogenesis, Mutagenesis, Impairment of Fertility

Gabapentin was given in the diet to mice at 200, 600, and 2000 mg/kg/day and to rats at 250, 1000, and 2000 mg/kg/day for 2 years. A statistically significant increase in the incidence of pancreatic acinar cell adenomas and carcinomas was found in male rats receiving the high dose; the no-effect dose for the occurrence of carcinomas was 1000 mg/kg/day. Peak plasma concentrations of gabapentin in rats receiving the high dose of 2000 mg/kg were 10 times higher than plasma concentrations in humans receiving 3600 mg per day, and in rats receiving 1000 mg/kg/day peak plasma concentrations were 6.5 times higher than in humans receiving 3600 mg/day. The pancreatic acinar cell carcinomas did not affect survival, did not metastasize and were not locally invasive. The relevance of this finding to carcinogenic risk in humans is unclear.

Studies designed to investigate the mechanism of gabapentin-induced pancreatic carcinogenesis in rats indicate that gabapentin stimulates DNA synthesis in rat pancreatic acinar cells in vitro and, thus, may be acting as a tumor promoter by enhancing mitogenic activity. It is not known whether gabapentin has the ability to increase cell proliferation in other cell types or in other species, including humans.

Gabapentin did not demonstrate mutagenic or genotoxic potential in three in vitro and four in vivo assays. It was negative in the Ames test and the in vitro HGPRT forward mutation assay in Chinese hamster lung cells; it did not produce significant increases in chromosomal aberrations in the in vitro Chinese hamster lung cell assay; it was negative in the in vivo chromosomal aberration assay and in the in vivo micronucleus test in Chinese hamster bone marrow; it was negative in the in vivo mouse micronucleus assay; and it did not induce unscheduled DNA synthesis in hepatocytes from rats given gabapentin.

No adverse effects on fertility or reproduction were observed in rats at doses up to 2000 mg/kg (approximately 5 times the maximum recommended human dose on a mg/m^2 basis).

Pregnancy

Pregnancy Category C

Gabapentin has been shown to be fetotoxic in rodents, causing delayed ossification of several bones in the skull, vertebrae, forelimbs, and hindlimbs. These effects occurred when pregnant mice received oral doses of 1000 or 3000 mg/kg/day during the period of organogenesis, or approximately 1 to 4 times the maximum dose of 3600 mg/day given to epileptic patients on a mg/m^2 basis. The no-effect level was 500 mg/kg/day or approximately ½ of the human dose on a mg/m^2 basis.

When rats were dosed prior to and during mating, and throughout gestation, pups from all dose groups (500, 1000 and 2000 mg/kg/day) were affected. These doses are equivalent to less than approximately 1 to 5 times the maximum human dose on a mg/m^2 basis. There was an increased incidence of hydroureter and/or hydronephrosis in rats in a study of fertility and general reproductive performance at 2000 mg/kg/day with no effect at 1000 mg/kg/day, in a teratology study at 1500 mg/kg/day with no effect at 300 mg/kg/day, and in a perinatal and postnatal study at all doses studied (500, 1000 and 2000 mg/kg/day). The doses at which the effects occurred are approximately 1 to 5 times the maximum human dose of 3600 mg/day on a mg/m^2 basis; the no-effect doses were approximately 3 times (Fertility and General Reproductive Performance study) and approximately equal to (Teratogenicity study) the maximum human dose on a mg/m^2 basis. Other than hydroureter and hydronephrosis, the etiologies of which are unclear, the incidence of malformations was not increased compared to controls in offspring of mice, rats, or rabbits given doses up to 50 times (mice), 30 times (rats), and 25 times (rabbits) the human daily dose on a mg/kg basis, or 4 times (mice), 5 times (rats), or 8 times (rabbits) the human daily dose on a mg/m^2 basis.

In a teratology study in rabbits, an increased incidence of postimplantation fetal loss occurred in dams exposed to 60, 300, and 1500 mg/kg/day, or less than approximately ¼ to 8 times the maximum human dose on a mg/m^2 basis. There are no adequate and well-controlled studies in pregnant women. This drug should be used during pregnancy only if the potential benefit justifies the potential risk to the fetus.

To provide information regarding the effects of in utero exposure to Neurontin, physicians are advised to recommend that pregnant patients taking Neurontin enroll in the North American Antiepileptic Drug (NAAED) Pregnancy Registry. This can be done by calling the toll free number 1-888-233-2334, and must be done by patients themselves. Information on the registry can also be found at the website http://www.aedpregnancyregistry.org/.

Use in Nursing Mothers

Gabapentin is secreted into human milk following oral administration. A nursed infant could be exposed to a maximum dose of approximately 1 mg/kg/day of gabapentin. Because the effect on the nursing infant is unknown, Neurontin should be used in women who are nursing only if the benefits clearly outweigh the risks.

Pediatric Use

Safety and effectiveness of Neurontin (gabapentin) in the management of postherpetic neuralgia in pediatric patients have not been established.

Effectiveness as adjunctive therapy in the treatment of partial seizures in pediatric patients below the age of 3 years has not been established (see CLINICAL PHARMACOLOGY, Clinical Studies).

Geriatric Use

The total number of patients treated with Neurontin in controlled clinical trials in patients with postherpetic neuralgia was 336, of which 102 (30%) were 65 to 74 years of age, and 168 (50%) were 75 years of age and older. There was a larger treatment effect in patients 75 years of age and older compared with younger patients who received the same dosage. Since gabapentin is almost exclusively eliminated by renal excretion, the larger treatment effect observed in patients ≥75 years may be a consequence of increased gabapentin exposure for a given dose that results from an age-related decrease in renal function. However, other factors cannot be excluded. The types and incidence of adverse events were similar across age groups except for peripheral edema and ataxia, which tended to increase in incidence with age.

Clinical studies of Neurontin in epilepsy did not include sufficient numbers of subjects aged 65 and over to determine whether they responded differently from younger subjects. Other reported clinical experience has not identified differences in responses between the elderly and younger patients. In general, dose selection for an elderly patient should be cautious, usually starting at the low end of the dosing range, reflecting the greater frequency of decreased hepatic, renal, or cardiac function, and of concomitant disease or other drug therapy.

This drug is known to be substantially excreted by the kidney, and the risk of toxic reactions to this drug may be greater in patients with impaired renal function. Because elderly patients are more likely to have decreased renal function, care should be taken in dose selection, and dose should be adjusted based on creatinine clearance values in these patients (see CLINICAL PHARMACOLOGY, ADVERSE REACTIONS, and DOSAGE AND ADMINISTRATION sections).

ADVERSE REACTIONS

Postherpetic Neuralgia

The most commonly observed adverse events associated with the use of Neurontin in adults, not seen at an equivalent frequency among placebo-treated patients, were dizziness, somnolence, and peripheral edema.

In the 2 controlled studies in postherpetic neuralgia, 16% of the 336 patients who received Neurontin and 9% of the 227 patients who received placebo discontinued treatment because of an adverse event. The adverse events that most frequently led to withdrawal in Neurontin-treated patients were dizziness, somnolence, and nausea.

Incidence in Controlled Clinical Trials

Table 3 lists treatment-emergent signs and symptoms that occurred in at least 1% of Neurontin-treated patients with postherpetic neuralgia participating in placebo-controlled trials and that were numerically more frequent in the Neurontin group than in the placebo group. Adverse events were usually mild to moderate in intensity.

TABLE 3. Treatment-Emergent Adverse Event Incidence in Controlled Trials in Postherpetic Neuralgia (Events in at least 1% of Neurontin-Treated Patients and Numerically More Frequent Than in the Placebo Group)
Body System/ | Neurontin | Placebo
Preferred Term | N=336 % | N=227 %
Body as a Whole
Asthenia | 5.7 | 4.8
Infection | 5.1 | 3.5
Headache | 3.3 | 3.1
Accidental injury | 3.3 | 1.3
Abdominal pain | 2.7 | 2.6
Digestive System
Diarrhea | 5.7 | 3.1
Dry mouth | 4.8 | 1.3
Constipation | 3.9 | 1.8
Nausea | 3.9 | 3.1
Vomiting | 3.3 | 1.8
Flatulence | 2.1 | 1.8
Metabolic and Nutritional Disorders
Peripheral edema | 8.3 | 2.2
Weight gain | 1.8 | 0.0
Hyperglycemia | 1.2 | 0.4
Nervous System
Dizziness | 28.0 | 7.5
Somnolence | 21.4 | 5.3
Ataxia | 3.3 | 0.0
Thinking abnormal | 2.7 | 0.0
Abnormal gait | 1.5 | 0.0
Incoordination | 1.5 | 0.0
Amnesia | 1.2 | 0.9
Hypesthesia | 1.2 | 0.9
Respiratory System
Pharyngitis | 1.2 | 0.4
Skin and Appendages
Rash | 1.2 | 0.9
Special Senses
Amblyopia [Reported as blurred vision] | 2.7 | 0.9
Conjunctivitis | 1.2 | 0.0
Diplopia | 1.2 | 0.0
Otitis media | 1.2 | 0.0

Other events in more than 1% of patients but equally or more frequent in the placebo group included pain, tremor, neuralgia, back pain, dyspepsia, dyspnea, and flu syndrome.

There were no clinically important differences between men and women in the types and incidence of adverse events. Because there were few patients whose race was reported as other than white, there are insufficient data to support a statement regarding the distribution of adverse events by race.

Epilepsy

The most commonly observed adverse events associated with the use of Neurontin in combination with other antiepileptic drugs in patients >12 years of age, not seen at an equivalent frequency among placebo-treated patients, were somnolence, dizziness, ataxia, fatigue, and nystagmus. The most commonly observed adverse events reported with the use of Neurontin in combination with other antiepileptic drugs in pediatric patients 3 to 12 years of age, not seen at an equal frequency among placebo-treated patients, were viral infection, fever, nausea and/or vomiting, somnolence, and hostility (see WARNINGS, Neuropsychiatric Adverse Events).

Approximately 7% of the 2074 patients >12 years of age and approximately 7% of the 449 pediatric patients 3 to 12 years of age who received Neurontin in premarketing clinical trials discontinued treatment because of an adverse event. The adverse events most commonly associated with withdrawal in patients >12 years of age were somnolence (1.2%), ataxia (0.8%), fatigue (0.6%), nausea and/or vomiting (0.6%), and dizziness (0.6%). The adverse events most commonly associated with withdrawal in pediatric patients were emotional lability (1.6%), hostility (1.3%), and hyperkinesia (1.1%).

Incidence in Controlled Clinical Trials

Table 4 lists treatment-emergent signs and symptoms that occurred in at least 1% of Neurontin-treated patients >12 years of age with epilepsy participating in placebo-controlled trials and were numerically more common in the Neurontin group. In these studies, either Neurontin or placebo was added to the patient's current antiepileptic drug therapy. Adverse events were usually mild to moderate in intensity.

The prescriber should be aware that these figures, obtained when Neurontin was added to concurrent antiepileptic drug therapy, cannot be used to predict the frequency of adverse events in the course of usual medical practice where patient characteristics and other factors may differ from those prevailing during clinical studies. Similarly, the cited frequencies cannot be directly compared with figures obtained from other clinical investigations involving different treatments, uses, or investigators. An inspection of these frequencies, however, does provide the prescribing physician with one basis to estimate the relative contribution of drug and nondrug factors to the adverse event incidences in the population studied.

TABLE 4. Treatment-Emergent Adverse Event Incidence in Controlled Add-On Trials In Patients >12 years of age (Events in at least 1% of Neurontin patients and numerically more frequent than in the placebo group)
Body System/ | Neurontin [Plus background antiepileptic drug therapy] | Placebo
Adverse Event | N=543 % | N=378 %
Body As A Whole
Fatigue | 11.0 | 5.0
Weight Increase | 2.9 | 1.6
Back Pain | 1.8 | 0.5
Peripheral Edema | 1.7 | 0.5
Cardiovascular
Vasodilatation | 1.1 | 0.3
Digestive System
Dyspepsia | 2.2 | 0.5
Mouth or Throat Dry | 1.7 | 0.5
Constipation | 1.5 | 0.8
Dental Abnormalities | 1.5 | 0.3
Increased Appetite | 1.1 | 0.8
Hematologic and Lymphatic Systems
Leukopenia | 1.1 | 0.5
Musculoskeletal System
Myalgia | 2.0 | 1.9
Fracture | 1.1 | 0.8
Nervous System
Somnolence | 19.3 | 8.7
Dizziness | 17.1 | 6.9
Ataxia | 12.5 | 5.6
Nystagmus | 8.3 | 4.0
Tremor | 6.8 | 3.2
Nervousness | 2.4 | 1.9
Dysarthria | 2.4 | 0.5
Amnesia | 2.2 | 0.0
Depression | 1.8 | 1.1
Thinking Abnormal | 1.7 | 1.3
Twitching | 1.3 | 0.5
Coordination Abnormal | 1.1 | 0.3
Respiratory System
Rhinitis | 4.1 | 3.7
Pharyngitis | 2.8 | 1.6
Coughing | 1.8 | 1.3
Skin and Appendages
Abrasion | 1.3 | 0.0
Pruritus | 1.3 | 0.5
Urogenital System
Impotence | 1.5 | 1.1
Special Senses
Diplopia | 5.9 | 1.9
Amblyopia [Amblyopia was often described as blurred vision.] | 4.2 | 1.1
Laboratory Deviations
WBC Decreased | 1.1 | 0.5

Other events in more than 1% of patients >12 years of age but equally or more frequent in the placebo group included: headache, viral infection, fever, nausea and/or vomiting, abdominal pain, diarrhea, convulsions, confusion, insomnia, emotional lability, rash, acne.

Among the treatment-emergent adverse events occurring at an incidence of at least 10% of Neurontin-treated patients, somnolence and ataxia appeared to exhibit a positive dose-response relationship.

The overall incidence of adverse events and the types of adverse events seen were similar among men and women treated with Neurontin. The incidence of adverse events increased slightly with increasing age in patients treated with either Neurontin or placebo. Because only 3% of patients (28/921) in placebo-controlled studies were identified as nonwhite (black or other), there are insufficient data to support a statement regarding the distribution of adverse events by race.

Table 5 lists treatment-emergent signs and symptoms that occurred in at least 2% of Neurontin-treated patients age 3 to 12 years of age with epilepsy participating in placebo-controlled trials and were numerically more common in the Neurontin group. Adverse events were usually mild to moderate in intensity.

TABLE 5. Treatment-Emergent Adverse Event Incidence in Pediatric Patients Age 3 to 12 Years in a Controlled Add-On Trial (Events in at least 2% of Neurontin patients and numerically more frequent than in the placebo group)
Body System/ | Neurontin [Plus background antiepileptic drug therapy] | Placebo
Adverse Event | N=119 % | N=128 %
Body As A Whole
Viral Infection | 10.9 | 3.1
Fever | 10.1 | 3.1
Weight Increase | 3.4 | 0.8
Fatigue | 3.4 | 1.6
Digestive System
Nausea and/or Vomiting | 8.4 | 7.0
Nervous System
Somnolence | 8.4 | 4.7
Hostility | 7.6 | 2.3
Emotional Lability | 4.2 | 1.6
Dizziness | 2.5 | 1.6
Hyperkinesia | 2.5 | 0.8
Respiratory System
Bronchitis | 3.4 | 0.8
Respiratory Infection | 2.5 | 0.8

Other events in more than 2% of pediatric patients 3 to 12 years of age but equally or more frequent in the placebo group included: pharyngitis, upper respiratory infection, headache, rhinitis, convulsions, diarrhea, anorexia, coughing, and otitis media.

Other Adverse Events Observed During All Clinical Trials

Clinical Trials in Adults and Adolescents (Except Clinical Trials in Neuropathic Pain)

Neurontin has been administered to 4717 patients >12 years of age during all adjunctive therapy clinical trials (except clinical trials in patients with neuropathic pain), only some of which were placebo-controlled. During these trials, all adverse events were recorded by the clinical investigators using terminology of their own choosing. To provide a meaningful estimate of the proportion of individuals having adverse events, similar types of events were grouped into a smaller number of standardized categories using modified COSTART dictionary terminology. These categories are used in the listing below. The frequencies presented represent the proportion of the 4717 patients >12 years of age exposed to Neurontin who experienced an event of the type cited on at least one occasion while receiving Neurontin. All reported events are included except those already listed in Table 4, those too general to be informative, and those not reasonably associated with the use of the drug.

Events are further classified within body system categories and enumerated in order of decreasing frequency using the following definitions: frequent adverse events are defined as those occurring in at least 1/100 patients; infrequent adverse events are those occurring in 1/100 to 1/1000 patients; rare events are those occurring in fewer than 1/1000 patients.

Body As A Whole: Frequent: asthenia, malaise, face edema; Infrequent: allergy, generalized edema, weight decrease, chill; Rare: strange feelings, lassitude, alcohol intolerance, hangover effect.

Cardiovascular System: Frequent: hypertension; Infrequent: hypotension, angina pectoris, peripheral vascular disorder, palpitation, tachycardia, migraine, murmur; Rare: atrial fibrillation, heart failure, thrombophlebitis, deep thrombophlebitis, myocardial infarction, cerebrovascular accident, pulmonary thrombosis, ventricular extrasystoles, bradycardia, premature atrial contraction, pericardial rub, heart block, pulmonary embolus, hyperlipidemia, hypercholesterolemia, pericardial effusion, pericarditis.

Digestive System: Frequent: anorexia, flatulence, gingivitis; Infrequent: glossitis, gum hemorrhage, thirst, stomatitis, increased salivation, gastroenteritis, hemorrhoids, bloody stools, fecal incontinence, hepatomegaly; Rare: dysphagia, eructation, pancreatitis, peptic ulcer, colitis, blisters in mouth, tooth discolor, perlèche, salivary gland enlarged, lip hemorrhage, esophagitis, hiatal hernia, hematemesis, proctitis, irritable bowel syndrome, rectal hemorrhage, esophageal spasm.

Endocrine System: Rare: hyperthyroid, hypothyroid, goiter, hypoestrogen, ovarian failure, epididymitis, swollen testicle, cushingoid appearance.

Hematologic and Lymphatic System: Frequent: purpura most often described as bruises resulting from physical trauma; Infrequent: anemia, thrombocytopenia, lymphadenopathy; Rare: WBC count increased, lymphocytosis, non-Hodgkin's lymphoma, bleeding time increased.

Musculoskeletal System: Frequent: arthralgia; Infrequent: tendinitis, arthritis, joint stiffness, joint swelling, positive Romberg test; Rare: costochondritis, osteoporosis, bursitis, contracture.

Nervous System: Frequent: vertigo, hyperkinesia, paresthesia, decreased or absent reflexes, increased reflexes, anxiety, hostility; Infrequent: CNS tumors, syncope, dreaming abnormal, aphasia, hypesthesia, intracranial hemorrhage, hypotonia, dysesthesia, paresis, dystonia, hemiplegia, facial paralysis, stupor, cerebellar dysfunction, positive Babinski sign, decreased position sense, subdural hematoma, apathy, hallucination, decrease or loss of libido, agitation, paranoia, depersonalization, euphoria, feeling high, doped-up sensation, psychosis; Rare: choreoathetosis, orofacial dyskinesia, encephalopathy, nerve palsy, personality disorder, increased libido, subdued temperament, apraxia, fine motor control disorder, meningismus, local myoclonus, hyperesthesia, hypokinesia, mania, neurosis, hysteria, antisocial reaction.

Respiratory System: Frequent: pneumonia; Infrequent: epistaxis, dyspnea, apnea; Rare: mucositis, aspiration pneumonia, hyperventilation, hiccup, laryngitis, nasal obstruction, snoring, bronchospasm, hypoventilation, lung edema.

Dermatological: Infrequent: alopecia, eczema, dry skin, increased sweating, urticaria, hirsutism, seborrhea, cyst, herpes simplex; Rare: herpes zoster, skin discolor, skin papules, photosensitive reaction, leg ulcer, scalp seborrhea, psoriasis, desquamation, maceration, skin nodules, subcutaneous nodule, melanosis, skin necrosis, local swelling.

Urogenital System: Infrequent: hematuria, dysuria, urination frequency, cystitis, urinary retention, urinary incontinence, vaginal hemorrhage, amenorrhea, dysmenorrhea, menorrhagia, breast cancer, unable to climax, ejaculation abnormal; Rare: kidney pain, leukorrhea, pruritus genital, renal stone, acute renal failure, anuria, glycosuria, nephrosis, nocturia, pyuria, urination urgency, vaginal pain, breast pain, testicle pain.

Special Senses: Frequent: abnormal vision; Infrequent: cataract, conjunctivitis, eyes dry, eye pain, visual field defect, photophobia, bilateral or unilateral ptosis, eye hemorrhage, hordeolum, hearing loss, earache, tinnitus, inner ear infection, otitis, taste loss, unusual taste, eye twitching, ear fullness; Rare: eye itching, abnormal accommodation, perforated ear drum, sensitivity to noise, eye focusing problem, watery eyes, retinopathy, glaucoma, iritis, corneal disorders, lacrimal dysfunction, degenerative eye changes, blindness, retinal degeneration, miosis, chorioretinitis, strabismus, eustachian tube dysfunction, labyrinthitis, otitis externa, odd smell.

Clinical trials in Pediatric Patients With Epilepsy

Adverse events occurring during epilepsy clinical trials in 449 pediatric patients 3 to 12 years of age treated with gabapentin that were not reported in adjunctive trials in adults are:

Body as a Whole: dehydration, infectious mononucleosis

Digestive System: hepatitis

Hemic and Lymphatic System: coagulation defect

Nervous System: aura disappeared, occipital neuralgia

Psychobiologic Function: sleepwalking

Respiratory System: pseudocroup, hoarseness

Clinical Trials in Adults With Neuropathic Pain of Various Etiologies

Safety information was obtained in 1173 patients during double-blind and open-label clinical trials including neuropathic pain conditions for which efficacy has not been demonstrated. Adverse events reported by investigators were grouped into standardized categories using modified COSTART IV terminology. Listed below are all reported events except those already listed in Table 3 and those not reasonably associated with the use of the drug.

Events are further classified within body system categories and enumerated in order of decreasing frequency using the following definitions: frequent adverse events are defined as those occurring in at least 1/100 patients; infrequent adverse events are those occurring in 1/100 to 1/1000 patients; rare events are those occurring in fewer than 1/1000 patients.

Body as a Whole: Infrequent: chest pain, cellulitis, malaise, neck pain, face edema, allergic reaction, abscess, chills, chills and fever, mucous membrane disorder; Rare: body odor, cyst, fever, hernia, abnormal BUN value, lump in neck, pelvic pain, sepsis, viral infection.

Cardiovascular System: Infrequent: hypertension, syncope, palpitation, migraine, hypotension, peripheral vascular disorder, cardiovascular disorder, cerebrovascular accident, congestive heart failure, myocardial infarction, vasodilatation; Rare: angina pectoris, heart failure, increased capillary fragility, phlebitis, thrombophlebitis, varicose vein.

Digestive System: Infrequent: gastroenteritis, increased appetite, gastrointestinal disorder, oral moniliasis, gastritis, tongue disorder, thirst, tooth disorder, abnormal stools, anorexia, liver function tests abnormal, periodontal abscess; Rare: cholecystitis, cholelithiasis, duodenal ulcer, fecal incontinence, gamma glutamyl transpeptidase increased, gingivitis, intestinal obstruction, intestinal ulcer, melena, mouth ulceration, rectal disorder, rectal hemorrhage, stomatitis.

Endocrine System: Infrequent: diabetes mellitus.

Hemic and Lymphatic System: Infrequent: ecchymosis, anemia; Rare: lymphadenopathy, lymphoma-like reaction, prothrombin decreased.

Metabolic and Nutritional: Infrequent: edema, gout, hypoglycemia, weight loss; Rare: alkaline phosphatase increased, diabetic ketoacidosis, lactic dehydrogenase increased.

Musculoskeletal: Infrequent: arthritis, arthralgia, myalgia, arthrosis, leg cramps, myasthenia; Rare: shin bone pain, joint disorder, tendon disorder.

Nervous System: Frequent: confusion, depression; Infrequent: vertigo, nervousness, paresthesia, insomnia, neuropathy, libido decreased, anxiety, depersonalization, reflexes decreased, speech disorder, abnormal dreams, dysarthria, emotional lability, nystagmus, stupor, circumoral paresthesia, euphoria, hyperesthesia, hypokinesia; Rare: agitation, hypertonia, libido increased, movement disorder, myoclonus, vestibular disorder.

Respiratory System: Infrequent: cough increased, bronchitis, rhinitis, sinusitis, pneumonia, asthma, lung disorder, epistaxis; Rare: hemoptysis, voice alteration.

Skin and Appendages: Infrequent: pruritus, skin ulcer, dry skin, herpes zoster, skin disorder, fungal dermatitis, furunculosis, herpes simplex, psoriasis, sweating, urticaria, vesiculobullous rash; Rare: acne, hair disorder, maculopapular rash, nail disorder, skin carcinoma, skin discoloration, skin hypertrophy.

Special Senses: Infrequent: abnormal vision, ear pain, eye disorder, taste perversion, deafness; Rare: conjunctival hyperemia, diabetic retinopathy, eye pain, fundi with microhemorrhage, retinal vein thrombosis, taste loss.

Urogenital System: Infrequent: urinary tract infection, dysuria, impotence, urinary incontinence, vaginal moniliasis, breast pain, menstrual disorder, polyuria, urinary retention; Rare: cystitis, ejaculation abnormal, swollen penis, gynecomastia, nocturia, pyelonephritis, swollen scrotum, urinary frequency, urinary urgency, urine abnormality.

Postmarketing and Other Experience

In addition to the adverse experiences reported during clinical testing of Neurontin, the following adverse experiences have been reported in patients receiving marketed Neurontin. These adverse experiences have not been listed above and data are insufficient to support an estimate of their incidence or to establish causation. The listing is alphabetized: angioedema, blood glucose fluctuation, breast hypertrophy, erythema multiforme, elevated liver function tests, fever, hyponatremia, jaundice, movement disorder, Stevens-Johnson syndrome.

Adverse events following the abrupt discontinuation of gabapentin have also been reported. The most frequently reported events were anxiety, insomnia, nausea, pain and sweating.

DRUG ABUSE AND DEPENDENCE

The abuse and dependence potential of Neurontin has not been evaluated in human studies.

OVERDOSAGE

A lethal dose of gabapentin was not identified in mice and rats receiving single oral doses as high as 8000 mg/kg. Signs of acute toxicity in animals included ataxia, labored breathing, ptosis, sedation, hypoactivity, or excitation.

Acute oral overdoses of Neurontin up to 49 grams have been reported. In these cases, double vision, slurred speech, drowsiness, lethargy and diarrhea were observed. All patients recovered with supportive care.

Gabapentin can be removed by hemodialysis. Although hemodialysis has not been performed in the few overdose cases reported, it may be indicated by the patient's clinical state or in patients with significant renal impairment.

DOSAGE AND ADMINISTRATION

Neurontin is given orally with or without food. Patients should be informed that, should they break the scored 600 or 800 mg tablet in order to administer a half-tablet, they should take the unused half-tablet as the next dose. Half-tablets not used within several days of breaking the scored tablet should be discarded.

If Neurontin dose is reduced, discontinued or substituted with an alternative medication, this should be done gradually over a minimum of 1 week (a longer period may be needed at the discretion of the prescriber).

Postherpetic Neuralgia

In adults with postherpetic neuralgia, Neurontin therapy may be initiated as a single 300-mg dose on Day 1, 600 mg/day on Day 2 (divided BID), and 900 mg/day on Day 3 (divided TID). The dose can subsequently be titrated up as needed for pain relief to a daily dose of 1800 mg (divided TID). In clinical studies, efficacy was demonstrated over a range of doses from 1800 mg/day to 3600 mg/day with comparable effects across the dose range. Additional benefit of using doses greater than 1800 mg/day was not demonstrated.

Epilepsy

Neurontin is recommended for add-on therapy in patients 3 years of age and older. Effectiveness in pediatric patients below the age of 3 years has not been established.

Patients >12 years of age: The effective dose of Neurontin is 900 to 1800 mg/day and given in divided doses (three times a day) using 300 or 400 mg capsules, or 600 or 800 mg tablets. The starting dose is 300 mg three times a day. If necessary, the dose may be increased using 300 or 400 mg capsules, or 600 or 800 mg tablets three times a day up to 1800 mg/day. Dosages up to 2400 mg/day have been well tolerated in long-term clinical studies. Doses of 3600 mg/day have also been administered to a small number of patients for a relatively short duration, and have been well tolerated. The maximum time between doses in the TID schedule should not exceed 12 hours.

Pediatric Patients Age 3–12 years: The starting dose should range from 10–15 mg/kg/day in 3 divided doses, and the effective dose reached by upward titration over a period of approximately 3 days. The effective dose of Neurontin in patients 5 years of age and older is 25–35 mg/kg/day and given in divided doses (three times a day). The effective dose in pediatric patients ages 3 and 4 years is 40 mg/kg/day and given in divided doses (three times a day) (see CLINICAL PHARMACOLOGY, Pediatrics.) Neurontin may be administered as the oral solution, capsule, or tablet, or using combinations of these formulations. Dosages up to 50 mg/kg/day have been well-tolerated in a long-term clinical study. The maximum time interval between doses should not exceed 12 hours.

It is not necessary to monitor gabapentin plasma concentrations to optimize Neurontin therapy. Further, because there are no significant pharmacokinetic interactions among Neurontin and other commonly used antiepileptic drugs, the addition of Neurontin does not alter the plasma levels of these drugs appreciably.

If Neurontin is discontinued and/or an alternate anticonvulsant medication is added to the therapy, this should be done gradually over a minimum of 1 week.

Dosage in Renal Impairment

Creatinine clearance is difficult to measure in outpatients. In patients with stable renal function, creatinine clearance (CCr) can be reasonably well estimated using the equation of Cockcroft and Gault:

for females CCr=(0.85)(140-age)(weight)/[(72)(SCr)]

for males CCr=(140-age)(weight)/[(72)(SCr)]

where age is in years, weight is in kilograms and SCr is serum creatinine in mg/dL.

Dosage adjustment in patients ≥12 years of age with compromised renal function or undergoing hemodialysis is recommended as follows (see dosing recommendations above for effective doses in each indication).

TABLE 6. Neurontin Dosage Based on Renal Function
Renal Function Creatinine Clearance (mL/min) | Total Daily Dose Range (mg/day) | Dose Regimen (mg)
≥60 | 900–3600 | 300 TID | 400 TID | 600 TID | 800 TID | 1200 TID
>30–59 | 400–1400 | 200 BID | 300 BID | 400 BID | 500 BID | 700 BID
>15–29 | 200–700 | 200 QD | 300 QD | 400 QD | 500 QD | 700 QD
15 [For patients with creatinine clearance <15 mL/min, reduce daily dose in proportion to creatinine clearance (e.g., patients with a creatinine clearance of 7.5 mL/min should receive one-half the daily dose that patients with a creatinine clearance of 15 mL/min receive).] | 100–300 | 100 QD | 125 QD | 150 QD | 200 QD | 300 QD
 |  | Post-Hemodialysis Supplemental Dose (mg) [Patients on hemodialysis should receive maintenance doses based on estimates of creatinine clearance as indicated in the upper portion of the table and a supplemental post-hemodialysis dose administered after each 4 hours of hemodialysis as indicated in the lower portion of the table.]
Hemodialysis |  | 125 | 150 | 200 | 250 | 350

The use of Neurontin in patients <12 years of age with compromised renal function has not been studied.

Dosage in Elderly

Because elderly patients are more likely to have decreased renal function, care should be taken in dose selection, and dose should be adjusted based on creatinine clearance values in these patients.

HOW SUPPLIED

Neurontin (gabapentin) capsules, tablets and oral solution are supplied as follows:

100 mg capsules;

White hard gelatin capsules printed with "PD" on one side and "Neurontin/100 mg" on the other; available in:
Bottles of 100: N 0071-0803-24
Unit dose 50's: N 0071-0803-40

300 mg capsules;

Yellow hard gelatin capsules printed with "PD" on one side and "Neurontin/300 mg" on the other; available in:
Bottles of 100: N 0071-0805-24
Unit dose 50's: N 0071-0805-40

400 mg capsules;

Orange hard gelatin capsules printed with "PD" on one side and "Neurontin/400 mg" on the other; available in:
Bottles of 100: N 0071-0806-24
Unit dose 50's: N 0071-0806-40

600 mg tablets;

White elliptical film-coated scored tablets debossed with "NT" and "16" on one side; available in:
Bottles of 100: N 0071-0513-24

800 mg tablets;

White elliptical film-coated scored tablets debossed with "NT" and "26" on one side; available in:
Bottles of 100: N 0071-0401-24

250 mg/5 mL oral solution;

Clear colorless to slightly yellow solution; each 5 mL of oral solution contains 250 mg of gabapentin; available in:
Bottles containing 470 mL: N0071-2012-23

Storage (Capsules)

Store at 25°C (77°F); excursions permitted to 15° – 30°C (59° – 86°F) [see USP Controlled Room Temperature].

Storage (Tablets)

Store at 25°C (77°F); excursions permitted to 15° – 30°C (59° – 86°F) [see USP Controlled Room Temperature].

Storage (Oral Solution)

Store refrigerated, 2°–8°C (36°–46°F)

MEDICATION GUIDE

NEURONTIN (Neu rŏn' tĭn)
(Gabapentin)

Capsules, Tablets, and Oral Solution

Read the Medication Guide before you start taking NEURONTIN and each time you get a refill. There may be new information. This information does not take the place of talking to your healthcare provider about your medical condition or treatment.

What is the most important information I should know about NEURONTIN?

Do not stop taking NEURONTIN without first talking to your healthcare provider.

Stopping NEURONTIN suddenly can cause serious problems.

NEURONTIN can cause serious side effects including:

1. Like other antiepileptic drugs, NEURONTIN may cause suicidal thoughts or actions in a very small number of people, about 1 in 500.
Call a healthcare provider right away if you have any of these symptoms, especially if they are new, worse, or worry you:

- thoughts about suicide or dying
- attempts to commit suicide
- new or worse depression
- new or worse anxiety
- feeling agitated or restless
- panic attacks
- trouble sleeping (insomnia)
- new or worse irritability
- acting aggressive, being angry, or violent
- acting on dangerous impulses
- an extreme increase in activity and talking (mania)
- other unusual changes in behavior or mood

How can I watch for early symptoms of suicidal thoughts and actions?

- Pay attention to any changes, especially sudden changes, in mood, behaviors, thoughts, or feelings.
- Keep all follow-up visits with your healthcare provider as scheduled.

Call your healthcare provider between visits as needed, especially if you are worried about symptoms.

Do not stop taking NEURONTIN without first talking to a healthcare provider.

- Stopping NEURONTIN suddenly can cause serious problems. Stopping a seizure medicine suddenly in a patient who has epilepsy can cause seizures that will not stop (status epilepticus).

Suicidal thoughts or actions can be caused by things other than medicines. If you have suicidal thoughts or actions, your healthcare provider may check for other causes.

2. Changes in behavior and thinking - Using NEURONTIN in children 3 to 12 years of age can cause emotional changes, aggressive behavior, problems with concentration, restlessness, changes in school performance, and hyperactivity.

What is NEURONTIN?

NEURONTIN is a prescription medicine used to treat:

- Pain from damaged nerves (postherpetic pain) that follows healing of shingles (a painful rash that comes after a herpes zoster infection) in adults.
- Partial seizures when taken together with other medicines in adults and children 3 years of age and older.

Who should not take NEURONTIN?

Do not take NEURONTIN if you are allergic to gabapentin or any of the other ingredients in NEURONTIN. See the end of this Medication Guide for a complete list of ingredients in NEURONTIN.

What should I tell my healthcare provider before taking NEURONTIN?

Before taking NEURONTIN, tell your healthcare provider if you:

- have or have had kidney problems or are on hemodialysis
- have or have had depression, mood problems, or suicidal thoughts or behavior
- are pregnant or plan to become pregnant. It is not known if NEURONTIN can harm your unborn baby. Tell your healthcare provider right away if you become pregnant while taking NEURONTIN. You and your healthcare provider will decide if you should take NEURONTIN while you are pregnant.
  - If you become pregnant while taking NEURONTIN, talk to your healthcare provider about registering with the North American Antiepileptic Drug (NAAED) Pregnancy Registry. The purpose of this registry is to collect information about the safety of antiepileptic drugs during pregnancy. You can enroll in this registry by calling 1-888-233-2334.
- are breast-feeding or plan to breast-feed. NEURONTIN can pass into breast milk. You and your healthcare provider should decide how you will feed your baby while you take NEURONTIN.

Tell your healthcare provider about all the medicines you take, including prescription and non-prescription medicines, vitamins, and herbal supplements.

Taking NEURONTIN with certain other medicines can cause side effects or affect how well they work. Do not start or stop other medicines without talking to your healthcare provider.

Know the medicines you take. Keep a list of them and show it to your healthcare provider and pharmacist when you get a new medicine.

How should I take NEURONTIN?

- Take NEURONTIN exactly as prescribed. Your healthcare provider will tell you how much NEURONTIN to take.
  - Do not change your dose of NEURONTIN without talking to your healthcare provider. If you break a tablet in half the unused half of the tablet should be taken at your next scheduled dose. Half tablets not used within several days of breaking should be thrown away. If taking capsules, always swallow them whole with plenty of water.
- NEURONTIN can be taken with or without food. If you take an antacid containing aluminum and magnesium, such as Maalox®, Mylanta®, Gelusil®, Gaviscon®, or Di-Gel®, you should wait at least 2 hours before taking your next dose of NEURONTIN.
- If you take too much NEURONTIN, call your healthcare provider or your local Poison Control Center right away.

What should I avoid while taking NEURONTIN?

- Do not drink alcohol or take other medicines that make you sleepy or dizzy while taking NEURONTIN without first talking with your healthcare provider. Taking NEURONTIN with alcohol or drugs that cause sleepiness or dizziness may make your sleepiness or dizziness worse.
- Do not drive, operate heavy machinery, or do other dangerous activities until you know how NEURONTIN affects you. NEURONTIN can slow your thinking and motor skills.

What are the possible side effects of NEURONTIN?

- See "What is the most important information I should know about NEURONTIN?"
- The most common side effects of NEURONTIN include:
  - dizziness
  - lack of coordination
  - viral infection
  - feeling drowsy
  - feeling tired
  - fever
  - jerky movements
  - difficulty with speaking
  - temporary loss of memory (amnesia)
  - tremor
  - difficulty with coordination
  - double vision
  - unusual eye movement

Tell your healthcare provider if you have any side effect that bothers you or that does not go away.

These are not all the possible side effects of NEURONTIN. For more information, ask your healthcare provider or pharmacist.

Call your doctor for medical advice about side effects. You may report side effects to FDA at 1-800-FDA-1088.

How should I store NEURONTIN?

- Store NEURONTIN Capsules between 59°F to 86°F (15°C to 30°C).
- Store NEURONTIN Tablets between 59°F to 86°F (15°C to 30°C).
- Store NEURONTIN Oral Solution in the refrigerator between 36°F to 46°F (2°C to 8°C).

Keep NEURONTIN and all medicines out of the reach of children.

General information about the safe and effective use of NEURONTIN

Medicines are sometimes prescribed for purposes other than those listed in a Medication Guide. Do not use NEURONTIN for a condition for which it was not prescribed. Do not give NEURONTIN to other people, even if they have the same symptoms that you have. It may harm them.

This Medication Guide summarizes the most important information about NEURONTIN. If you would like more information, talk with your healthcare provider. You can ask your healthcare provider or pharmacist for information about NEURONTIN that was written for healthcare professionals.

For more information about NEURONTIN, go to http://www.pfizer.com. For medical inquiries or to report side effects regarding Neurontin, please call 1-800-438-1985.

What are the ingredients in NEURONTIN?

Active ingredient: gabapentin

Inactive ingredients in the capsules: lactose, cornstarch, and talc.

The 100-mg capsule shell also contains: gelatin and titanium dioxide.

The 300-mg capsule shell also contains: gelatin, titanium dioxide, and yellow iron oxide.

The 400-mg capsule shell also contains: gelatin, red iron oxide, titanium dioxide, and yellow iron oxide. The imprinting ink contains FD and C Blue No. 2 and titanium dioxide.

Inactive ingredients in the tablets: poloxamer 407, copolyvidonum, cornstarch, magnesium stearate, hydroxypropyl cellulose, talc, candelilla wax, and purified water.

Inactive ingredients in the oral solution: glycerin, xylitol, purified water, and artificial flavor.

This Medication Guide has been approved by the U.S. Food and Drug Administration.

NEURONTIN 400MG LABEL